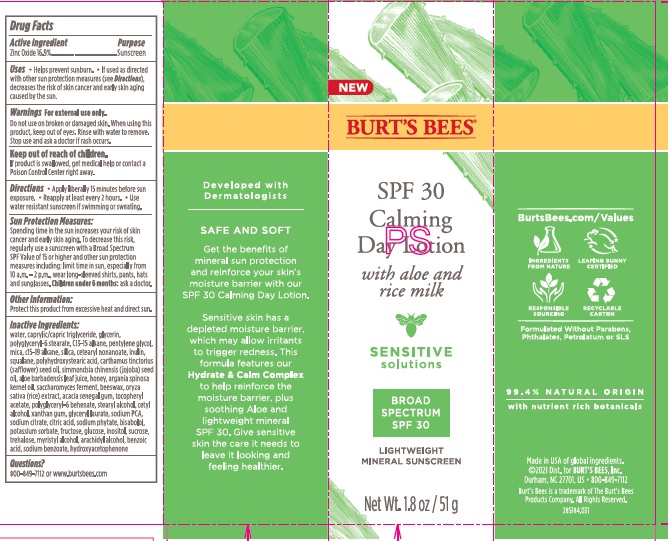 DRUG LABEL: Burts Bees Calming Day
NDC: 26052-492 | Form: LOTION
Manufacturer: Burts Bees
Category: otc | Type: HUMAN OTC DRUG LABEL
Date: 20241203

ACTIVE INGREDIENTS: ZINC OXIDE 16.9 g/100 g
INACTIVE INGREDIENTS: SODIUM PYRROLIDONE CARBOXYLATE; YELLOW WAX; ACACIA; SODIUM CITRATE; CITRIC ACID MONOHYDRATE; LEVOMENOL; HEXASODIUM PHYTATE; HONEY; RICE GERM; WATER; MEDIUM-CHAIN TRIGLYCERIDES; C13-15 ALKANE; PENTYLENE GLYCOL; MICA; C15-19 ALKANE; SILICON DIOXIDE; CETEARYL NONANOATE; INULIN; SQUALANE; SAFFLOWER OIL; CETOSTEARYL ALCOHOL; JOJOBA OIL; POLYHYDROXYSTEARIC ACID (2300 MW); ARGAN OIL; .ALPHA.-TOCOPHEROL ACETATE; ALOE; HYDROXYACETOPHENONE; XANTHAN GUM; POLYGLYCERYL-6 BEHENATE; GLYCERYL LAURATE

Burt's Bees Calming Day Lotion SPF30

Active Ingredient

Zinc Oxide 16.9%

Purpose

Sunscreen

Uses

- Helps prevent sunburn
- If used as directed with other sun protection measures (see Directions), decreases the risk of skin cancer and early skin aging caused by the sun.

Warnings

For external use only.

Do not use on broken or damaged skin.

When using this product, keep out of eyes. Rinse with water to remove.

Stop use and ask a doctor if rash occurs.

Keep out of reach of children.

If product is swalloed, get medical help or contact a Poison Control Center right away.

Directions

- Apply liberally 15 minutes before sun exposure
- Reapply

Sun Protection Measures

Spending time in the sun increases your risk of skin cancer and early skin aging. To decrease this risk, regularly us a sunscreen with a Broad Spectrum SPF value of 15 or higher and other sun protection measures including: limit time in sun, especially from 10a.m.-2p.m., wear long-sleeved shirts, pants, hats and sunglasses . Children under 6 months: ask a doctor.

Other Information

Protect this product from excessive hear and direct sun.

Inactive Ingredients:

water, caprylic/capric triglyceride, glycerin, polyglyceryl-6 stearate, C13-15 alkane, pentylene glycol, mica, c15-19 alkane, silica, cetearyl nonanoate, inulin, squalane, polyhydroxystearic acid, carthamus tinctorius (safflower) seed oil, simmondsia chinensis (jojoba) seed oil, aloe barbadensis leaf juice, honey, argania spinosa kernel oil, saccharomyces ferment, beeswax, oryza sativa (rice) extract, acacia senegal gum, tocopheryl acetate, polyglyceryl-6 behenate, stearyl alcohol, cetyl alcohol, xanthan gum, glyceryl laurate, sodium PCA, sodium citrate, citric acid, sodium phytate, bisabolol, potassium sorbate, fructose, glucose, inositol, sucrose, trehalose, myristyl alcohol, arachidyl alcohol, benzoic acid, sodium benxoate, hydroxyacetophenone